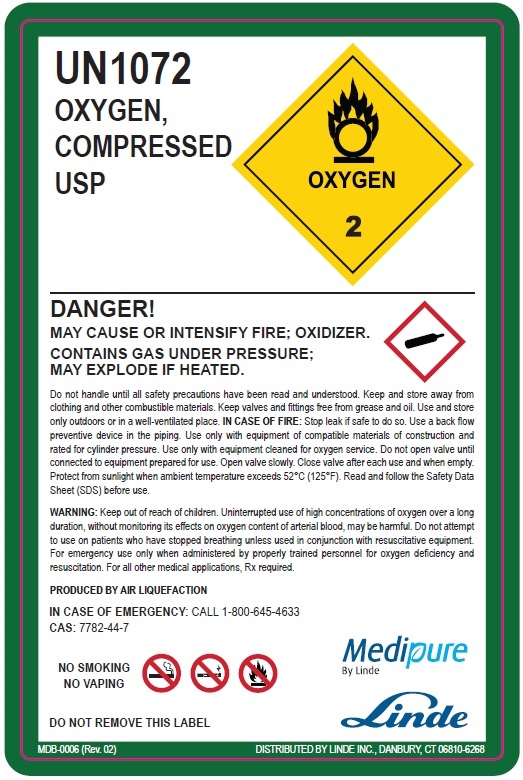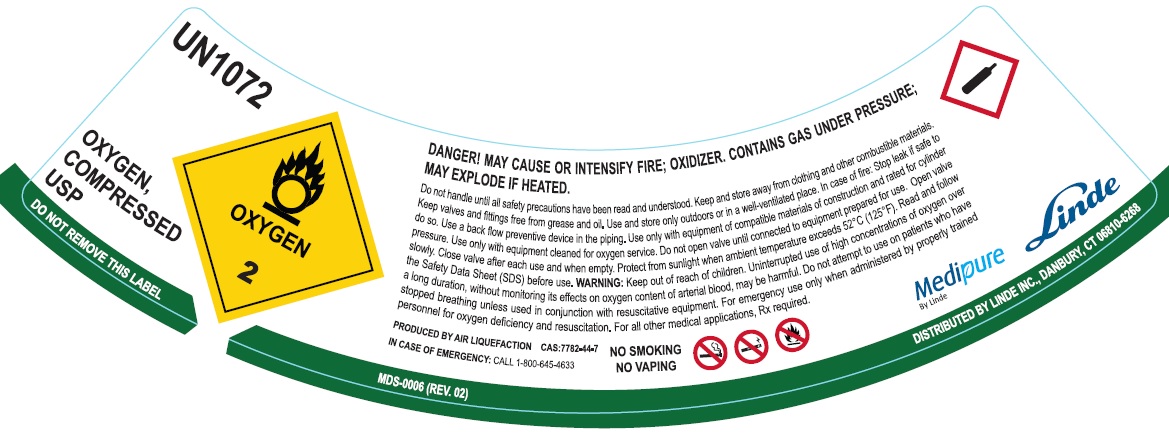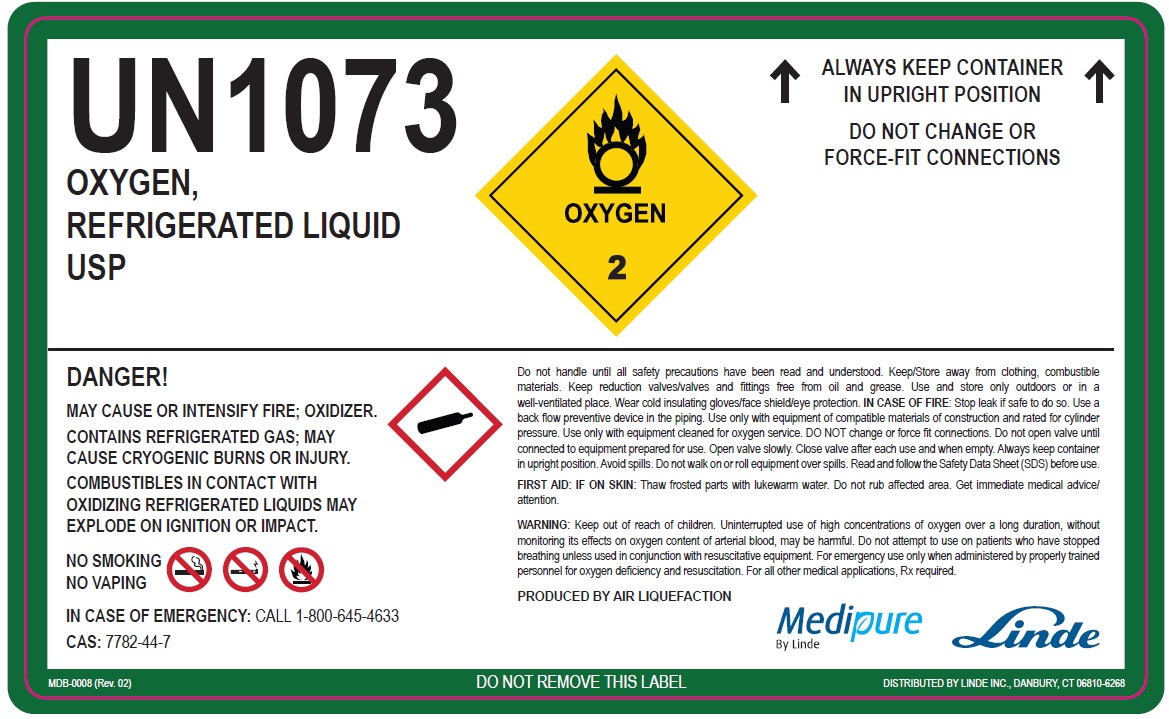 DRUG LABEL: Oxygen
NDC: 59579-001 | Form: GAS
Manufacturer: Linde Gas & Equipment Inc.
Category: prescription | Type: HUMAN PRESCRIPTION DRUG LABEL
Date: 20260107

ACTIVE INGREDIENTS: OXYGEN 990 mL/1 L

Oxygen - Human - 001

Oxygen Shoulder Label

UN1072

OXYGEN,

COMPRESSED USP

DANGER!
MAY CAUSE OR INTENSIFY FIRE; OXIDIZER. CONTAINS GAS UNDER PRESSURE;
MAY EXPLODE IF HEATED

Do not handle until all safety precautions have been read and understood. Keep/Store away from clothing, combustible materials.

Keep valves and fittings free from grease and oil. Use and store only outdoors or in a well-ventilated place. In case of fire: Stop leak if safe to do so. Use a backflow prevention device in any piping. Use onlu with equipment of compatible materials of construction and rated for cylinder pressure. Use only with equipment cleaned for oxigen service. Do not open valve until connected to equipment prepared for use. Open valve slowly. Close valve after each use and when empty. Protect from sunlight when ambient temperature exceeds 52°C (125°F). Read and follow the Safety Data Sheet (SDS) before use. WARNING: Keep out of reach of children. Uninterupted use of high concentrations of oxygen over a long duration, without monitoring its effects on oxygen content of arterial blood, may be harmful. Do not attempt to use on patients who have stopped breathing unless used in conjuction with resucitative equipment. For emergency use only when administerend by properly trained personnel for oxygen deficiency and resucitation. For all other medical applications, Rx required.

PRODUCED BY AIR LIQUEFACTION CAS 7782-44-7

IN CASE OF EMERGENCY: CALL 1-800-645-4633

NO SMOKING

NO VAPING

Medipure

By Linde

MDS-0006 (REV. 02) DISTRIBUTED BY LINDE INC., DANBURY, CT 06810-6268

Oxygen Body Label

UN1072
OXYGEN,
COMPRESSED
USP

DANGER!
MAY CAUSE OR INTENSIFY FIRE; OXIDIZER.
CONTAINS GAS UNDER PRESSURE;
MAY EXPLODE IF HEATED.

Do not handle until all safety precautions have been read and understood. Keep and store away from clothing and other combustible materials. Keep valves and fittings free from grease and oil. Use and store only outdoors or in a well-ventilated place. IN CASE OF FIRE: Stop leak if safe to do so. Use a back flow preventive device in the piping. Use only with equipment cleaned for oxygen services. Do not open valve until connected to equipment prepared for use. Open valve slowly. Close valve after each use and when empty. Protect from sunlight when ambient temperature exceeds 52˚⁰C (125⁰F). Read and follow the Safety Data Sheet (SDS) before use.
WARNING: Keep out of reach of children. Uninterrupted use of high concentrations of oxygen over long duration, without monitoring its effects on oxygen content of arterial blood, may be harmful. Do not attempt to use on patients who have stopped breathing unless in conjunction with resuscitative equipment. For emergency use only when administered by properly trained personnel for oxygen deficiency and resuscitation. For all other medical application, Rx required.

PRODUCED BY AIR LIQUEFACTION
IN CASE OF EMERGENCY: CALL 1-800-645-4633
CAS: 7782-44-7
NO SMOKING
NO VAPING
DO NOT REMOVE THIS LABEL
Medipure
By Linde
Linde
MDB-0006 (Rev. 02) DISTRIBUTED BY LINDE INC., DANBURY, CT 06810-6268

Oxygen Refrigerated

UN1073
OXYGEN,
REFRIGERATED LIQUID
USP
↑ALWAYS KEEP CONTAINER
IN UPRIGHT POSITION
DO NOT CHANGE OR
FORCE-FIT CONNECTIONS↑

DANGER!
MAY CAUSE OR INTENSIFY FIRE; OXIDIZER.
CONTAINS REFRIGERATED GAS; MAY CAUSE CRYOGENIC BURNS OR INJURY.
COMBUSTIBLES IN CONTACT WITH OXIDIZING REFRIGERATED LIQUIDS MAY EXPLODE ON IGNITION OR IMPACT.
NO SMOKING
NO VAPING

IN CASE OF EMERGENCY: CALL 1-800-645-4633
CAS: 7782-44-7

Do not handle until all safety precautions have been read and understood. Keep/Store away from clothing, combustible materials. Keep reduction valves/valves and fittings free from oil and grease. Use and store only outdoors or in a
well-ventilated place. Wear cold insulating gloves/face shield/eye protection. IN CASE OF FIRE: Stop leak if safe to do so. Use a back flow preventive device in the piping. Use only with equipment of compatible materials of construction and rated for cylinder pressure. Use only with equipment cleaned for oxygen service. DO NOT change or force fit connections. Do not open valve until connected to equipment prepared for use. Open valve slowly. Close valve after each use and when empty. Always keep container in upright position. Avoid spills. Do not walk on or roll equipment over spills. Read and follow the Safety Data Sheet (SDS) before use.

FIRST AID: IF ON SKIN: Thaw frosted parts with lukewarm water. Do not rub affected area. Get immediate medical advice/attention.
WARNING: Keep out of reach of children. Uninterrupted use of high concentrations of oxygen over a long duration, without monitoring its effects on oxygen content of arterial blood, may be harmful. Do not attempt to use on patients who have stopped breathing unless used in conjunction with resuscitative equipment. For emergency use only when administered by properly trained personnel for oxygen deficiency and resuscitation. For all other medical applications, Rx required.

PRODUCED BY AIR LIQUEFACTION
Medipure
By Linde
Linde
MDB-0008 (Rev. 02)
DO NOT REMOVE THIS LABEL
DISTRIBUTED BY LINDE INC., DANBURY, CT 06810-6268